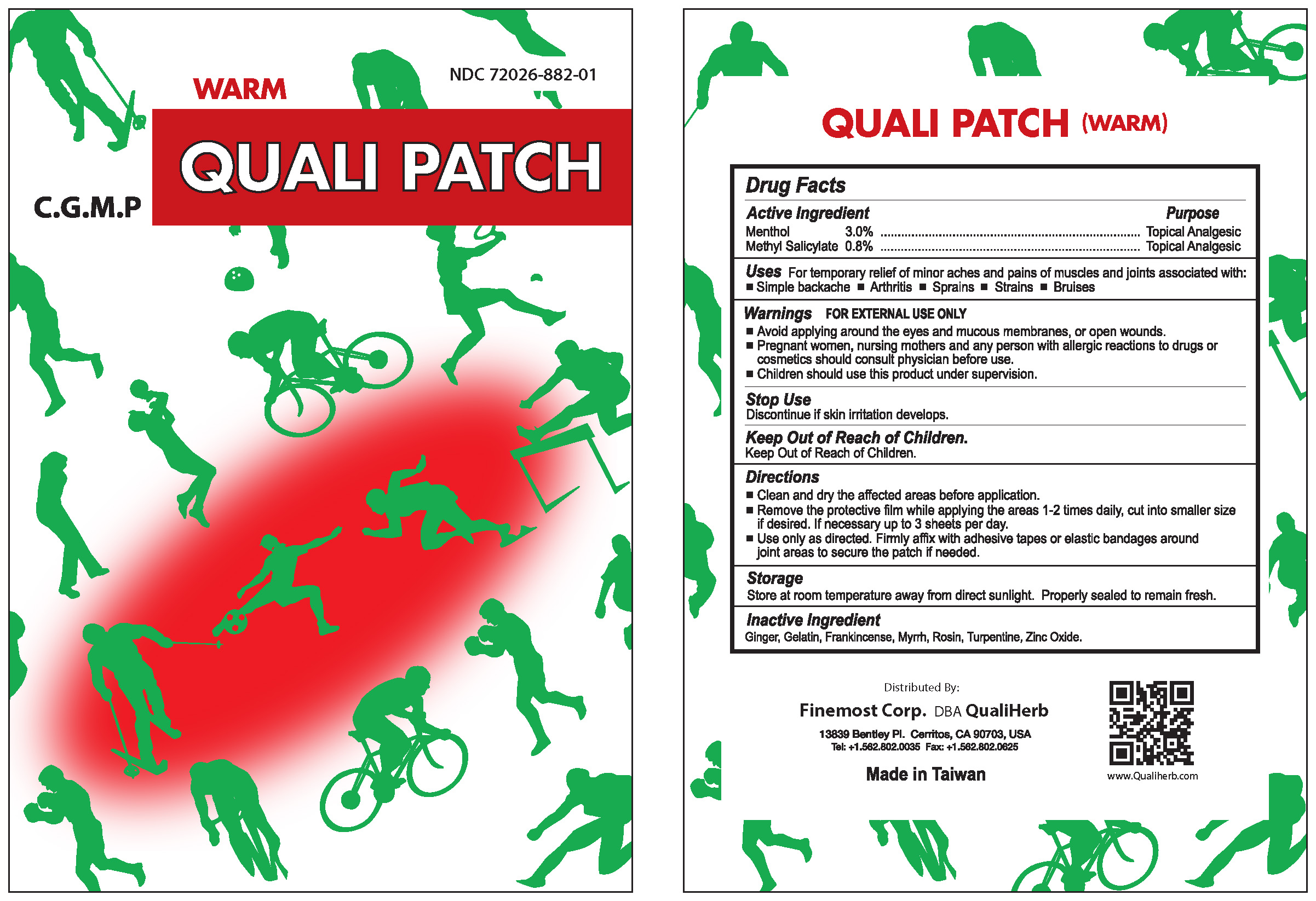 DRUG LABEL: Quali Patch Warm
NDC: 72026-882 | Form: PATCH
Manufacturer: Finemost Corporation
Category: otc | Type: HUMAN OTC DRUG LABEL
Date: 20230601

ACTIVE INGREDIENTS: MENTHOL 3 g/100 g; METHYL SALICYLATE 0.8 g/100 g
INACTIVE INGREDIENTS: GINGER; GELATIN; FRANKINCENSE; MYRRH; ROSIN; TURPENTINE; ZINC OXIDE

Finemost Corporation

ACTIVE INGREDIENTS

Menthol 3.0%

Methyl Salicylate 0.8%

Purpose

Menthol Topical Analgesic
Methyl Salicylate Topical Analgesic

Uses

For temporary relief of minor aches and pains of muscles and joints associated with:
Simple backache
Arthritis
Sprains
Strains
Bruises

Warnings

1. For external use only. Avoid applying around the eyes and mucous membranes, or open wounds.
2. Pregnant women, nursing mothers and any person with allergic reactions to drugs or cosmetics should consult physician before use. Children should use this product under supervision.

Stop Use

Discontinue if skin irritation develops.

Keep Out of Reach of Children.

Directions

1. Clean and dry the affected areas before application.
2. Remove the protective film while applying the areas 1-2 times daily, cut into smaller size if desired. If necessary up to 3 sheets per day.
3. Use only as directed. Firmly affix with adhesive tapes or elastic bandages around joint areas to secure the patch if needed.

Storage

Store at room temperature away from direct sunlight. Properly sealed to remain fresh.

Inactive Ingredients

Ginger, Gelatin, Frankincense, Myrrh, Rosin, Turpentine, Zinc Oxide

U.S. Sole Agent

Finemost Corp., Qualiherb

Cerritos, Ca 90703

Tel: (562)802-0035

Fax: (562)802-0625

Made in Taiwan